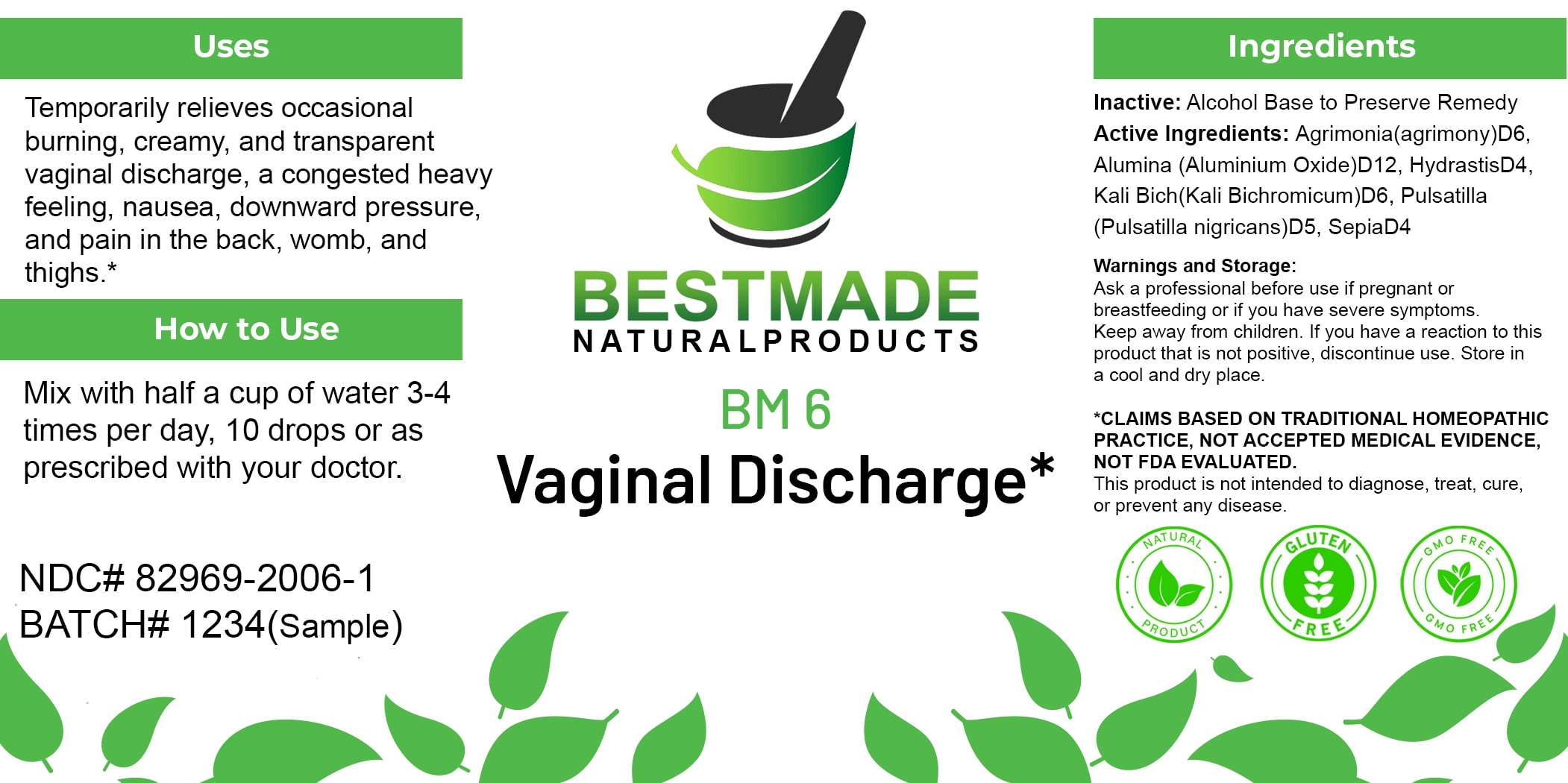 DRUG LABEL: Bestmade Natural Products BM6
NDC: 82969-2006 | Form: LIQUID
Manufacturer: Bestmade Natural Products
Category: homeopathic | Type: HUMAN OTC DRUG LABEL
Date: 20250122

ACTIVE INGREDIENTS: ALUMINUM OXIDE 30 [hp_C]/30 [hp_C]; GOLDENSEAL 30 [hp_C]/30 [hp_C]; PULSATILLA VULGARIS 30 [hp_C]/30 [hp_C]; SEPIA OFFICINALIS JUICE 30 [hp_C]/30 [hp_C]; POTASSIUM DICHROMATE 30 [hp_C]/30 [hp_C]; AGRIMONIA EUPATORIA 30 [hp_C]/30 [hp_C]
INACTIVE INGREDIENTS: ALCOHOL 30 [hp_C]/30 [hp_C]

BM6

DOSAGE AND ADMINISTRATION

How to Use

Mix with half a cup of water 3-4 times per day, 10 drops or as prescribed with your doctor.

Inactive:

Alcohol Base to Preserve Product

INDICATIONS AND USAGE

Temporarily relieves occasional burning, creamy, and transparent vaginal discharge, a congested heavy feeling, nausea, downward pressure, and pain in the back, womb, and thighs.*

*Claims Based on Traditional Homeopathic Practice, Not Accepted Medical Evidence, Not FDA Evaluated.

This product is not intended to diagnose, treat, cure, or prevent any disease.

Active Ingredients:

Agrimonia (agrimony)D6, Alumina (Aluminium Oxide)D12, HydrastisD4, Kali Bich (Kali Bichromicum)D6, Pulsatilla (Pulsatilla nigricans)D5, SepiaD4

KEEP OUT OF REACH OF CHILDREN

Warnings and Storage:

Ask a professional before use if pregnant or breastfeeding or if you have severe symptoms. Keep away from children. If you have a reaction to this product that is not positive, discontinue use. Store in a cool and dry place.

PURPOSE

Temporarily relieves occasional burning, creamy, and transparent vaginal discharge, a congested heavy feeling, nausea, downward pressure, and pain in the back, womb, and thighs.*

*Claims Based on Traditional Homeopathic Practice, Not Accepted Medical Evidence, Not FDA Evaluated.

This product is not intended to diagnose, treat, cure, or prevent any disease.

Warnings and Storage:

Ask a professional before use if pregnant or breastfeeding or if you have severe symptoms. Keep away from children. If you have a reaction to this product that is not positive, discontinue use. Store in a cool and dry place.

Claims Based on Traditional Homeopathic Practice, Not Accepted Medical Evidence, Not FDA Evaluated.

This product is not intended to diagnose, treat, cure, or prevent any disease.

Entire package label